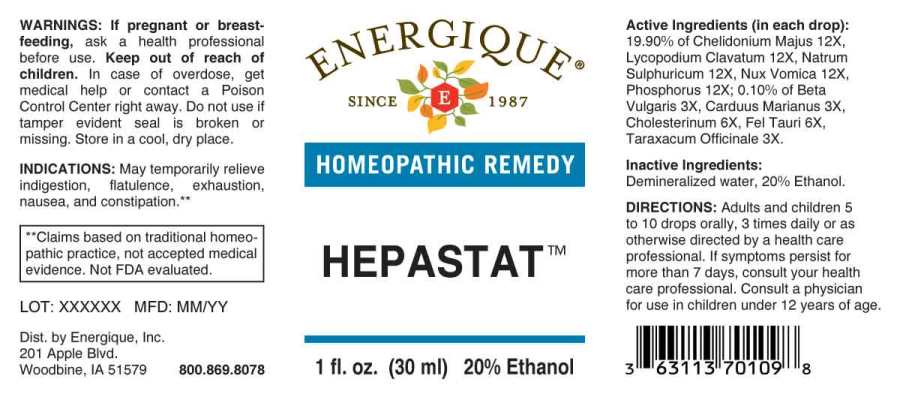 DRUG LABEL: Hepastat
NDC: 44911-0070 | Form: LIQUID
Manufacturer: Energique, Inc.
Category: homeopathic | Type: HUMAN OTC DRUG LABEL
Date: 20250519

ACTIVE INGREDIENTS: BETA VULGARIS WHOLE 3 [hp_X]/1 mL; SILYBUM MARIANUM SEED 3 [hp_X]/1 mL; TARAXACUM OFFICINALE 3 [hp_X]/1 mL; CHOLESTEROL 6 [hp_X]/1 mL; BOS TAURUS BILE 6 [hp_X]/1 mL; CHELIDONIUM MAJUS WHOLE 12 [hp_X]/1 mL; LYCOPODIUM CLAVATUM SPORE 12 [hp_X]/1 mL; SODIUM SULFATE 12 [hp_X]/1 mL; STRYCHNOS NUX-VOMICA SEED 12 [hp_X]/1 mL; PHOSPHORUS 12 [hp_X]/1 mL
INACTIVE INGREDIENTS: WATER; ALCOHOL

DRUG FACTS:

ACTIVE INGREDIENTS:

(in each drop): 19.90% of Chelidonium Majus 12X, Lycopodium Clavatum 12X, Natrum Sulphuricum 12X, Nux Vomica 12X, Phosphorus 12X; 0.10% of Beta Vulgaris 3X, Carduus Marianus 3X, Cholesterinum 6X, Fel Tauri 6X, Taraxacum Officinale 3X.

INDICATIONS:

May temporarily relieve indigestion, flatulence, exhaustion, nausea and constipation.**

**Claims based on traditional homeopathic practice, not accepted medical evidence. Not FDA evaluated.

WARNINGS:

If pregnant or breast-feeding, ask a health professional before use.

Keep out of reach of children. In case of overdose, get medical help or contact a Poison Control Center right away.

Do not use if tamper evident seal is broken or missing. Store in a cool, dry place.

Keep out of reach of children. In case of overdose, get medical help or contact a Poison Control Center right away.

DIRECTIONS:

Adults and children 5 to 10 drops orally, 3 times daily or as otherwise directed by a health care professional. If symptoms persist for more than 7 days, consult your health care professional. Consult a physician for use in children under 12 years of age.

INACTIVE INGREDIENTS

Demineralized water, 20% Ethanol.

INDICATIONS:

May temporarily relieve indigestion, flatulence, exhaustion, nausea and constipation.**

**Claims based on traditional homeopathic practice, not accepted medical evidence. Not FDA evaluated.

QUESTIONS

Dist. by Energique, Inc.

201 Apple Blvd

Woodbine, IA 51579

800-869-8078

PACKAGE LABEL DISPLAY:

ENERGIQUE

SINCE 1987

HOMEOPATHIC REMEDY

HEPASTAT

1 fl. oz. (30 ml)